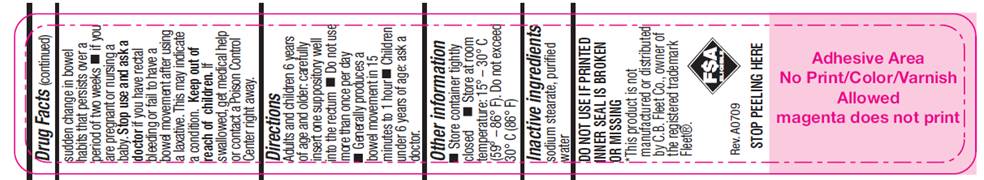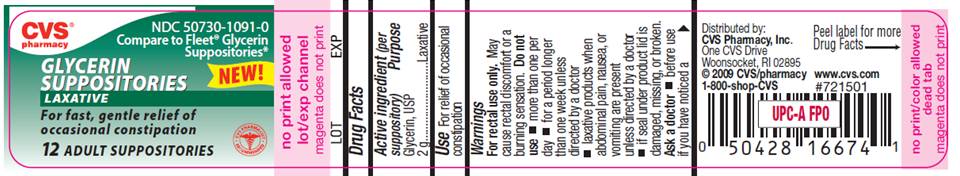 DRUG LABEL: Glycerin
NDC: 50730-1091 | Form: SUPPOSITORY
Manufacturer: H and P Industries, Inc. dba Triad Group
Category: otc | Type: HUMAN OTC DRUG LABEL
Date: 20091207

ACTIVE INGREDIENTS: glycerin 2 g/1 1
INACTIVE INGREDIENTS: sodium stearate; water

DRUG FACTS

ACTIVE INGREDIENT

Glycerin, USP 2g

PURPOSE

Laxative

USE

For relief of occasional constipation

WARNINGS

For rectal use only. May cause rectal discomfort or a burning sensation.

Do not use

- more than one per day
- for a period of longer than one week unless directed by a doctor
- laxative products when abdominal pain, nausea, or vomiting are present unless directed by a doctor
- if seal under product lid is damaged, missing or broken.

Ask a doctor before use

- if you have noticed a sudden change in bowel habits that persist over a period of two weeks
- if you are pregnant or nursing a baby

Stop use and ask a doctor

if you have rectal bleeding or fail to have a bowel movement after using a laxative. This may indicate a condition.

Keep out of reach of children

If swallowed, get medical help or contact a Poison Control Center right away.

DIRECTIONS

- Adults and children 6 years of age and older: carefully insert one suppository well into the rectum
- Do not use more than once per day
- Generally produces a bowel movement in 15 minutes to 1 hour
- Children under 6 years of age: ask a doctor.

OTHER INFORMATION

- Store container tightly closed
- Store at room temperature: 15°- 30° C (59° - 86° F). Do not exceed 30° C (86° F).

INACTIVE INGREDIENTS

sodium stearate, purified water

PACKAGE LABEL

CVS pharmacy
NDC 50730-1091-0
Compare to Fleet Glycerin Suppositories
NEW!
GLYCERIN
SUPPOSITORIES
LAXATIVE
For fast, gentle relief of
occasional constipation
12 ADULT SUPPOSITORIES
Distributed by CVS Pharmacy, Inc.
One CVS Drive
Woonsocket, RI 02895

©CVS/pharmacy
1-800-shop-CVS
www.cvs.com
#721501

DO NOT USE IF PRINTED
INNER SEAL IS BROKEN
OR MISSING
This product is not
manufactured or distributed
by C.B.Fleet co., owner of
the registered trademark
Fleet®.